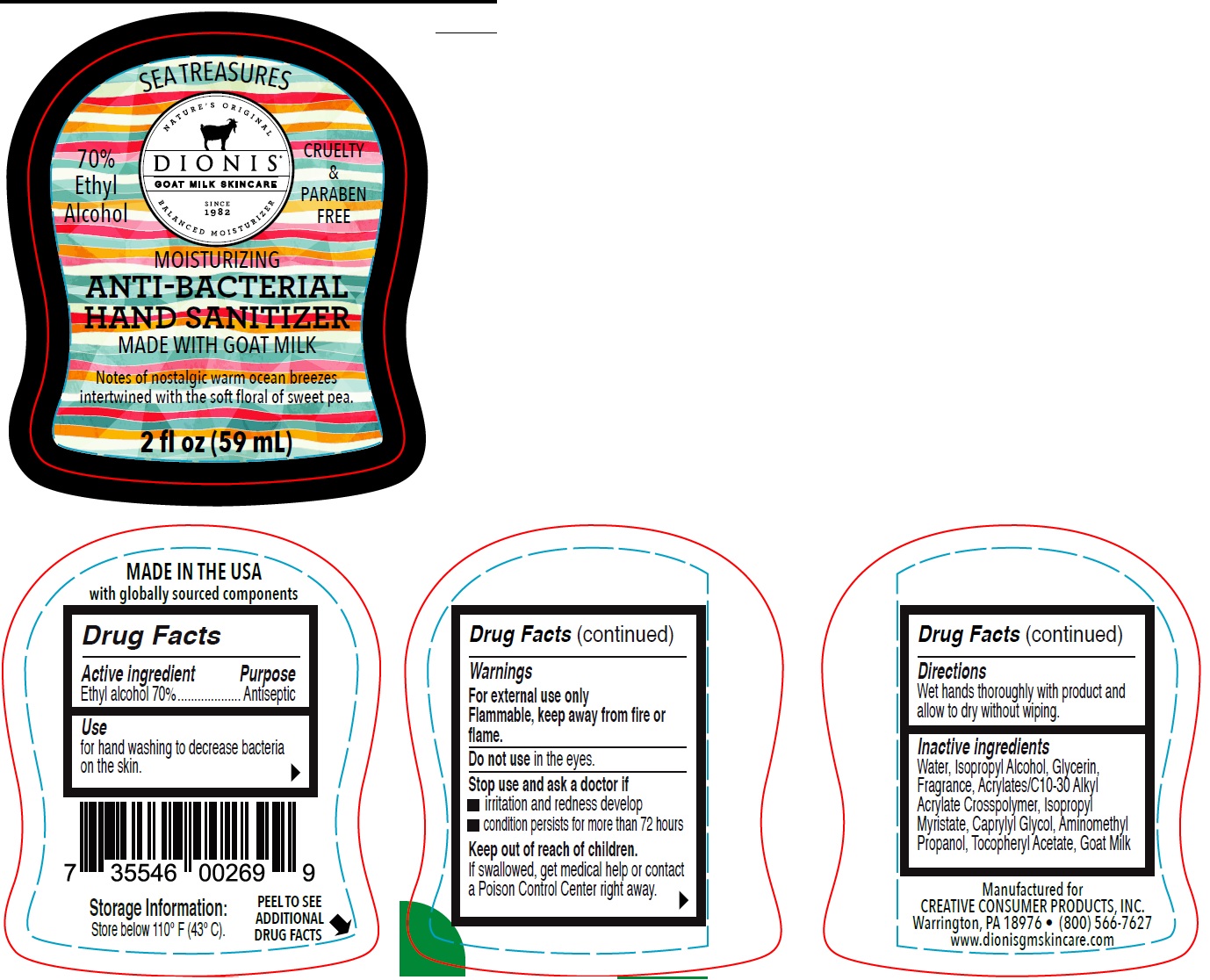 DRUG LABEL: Anti-Bacterial Hand Sanitizer with Goat Milk Sea Treasures
NDC: 74028-003 | Form: LIQUID
Manufacturer: Creative Consumer Products, Inc.
Category: otc | Type: HUMAN OTC DRUG LABEL
Date: 20210729

ACTIVE INGREDIENTS: ALCOHOL 70 mL/100 mL
INACTIVE INGREDIENTS: WATER; ISOPROPYL ALCOHOL; GLYCERIN; CARBOMER INTERPOLYMER TYPE A (ALLYL SUCROSE CROSSLINKED); ISOPROPYL MYRISTATE; CAPRYLYL GLYCOL; AMINOMETHYLPROPANOL; .ALPHA.-TOCOPHEROL ACETATE; GOAT MILK

Anti-Bacterial Hand Sanitizer with Goat Milk Sea Treasures

Active ingredient

Ethyl alcohol 70%

Purpose

Antiseptic

Use

for hand washing to decrease bacteria on the skin.

Warnings

For external use only Flammable, keep away from fire or flame.

Do not use

in the eyes.

Stop use and ask a doctor if

- irritation and redness develop
- condition persists for more than 72 hours

Keep out of reach of children.

If swallowed, get medical help or contact a Poison Control Center right away.

Directions

Wet hands thoroughly with product and allow to dry without wiping.

Inactive ingredients

Water, Isopropyl Alcohol, Glycerin, Fragrance, Acrylates/C10-30 Alkyl Acrylate Crosspolymer, Isopropyl Myristate, Caprylyl Glycol, Aminomethyl Propanol, Tocopheryl Acetate, Goat Milk